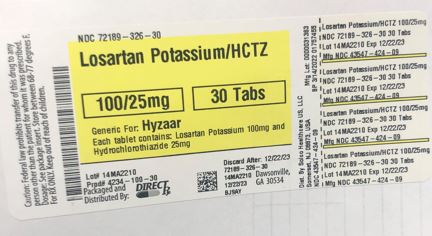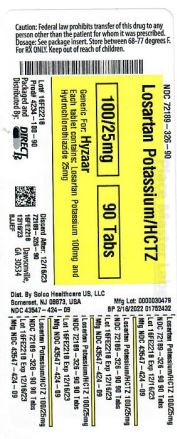 DRUG LABEL: LOSARTAN POTASSIUM AND HYDROCHLOROTHIAZIDE
NDC: 72189-326 | Form: TABLET, FILM COATED
Manufacturer: Direct Rx
Category: prescription | Type: HUMAN PRESCRIPTION DRUG LABEL
Date: 20250121

ACTIVE INGREDIENTS: LOSARTAN POTASSIUM 100 mg/1 1; HYDROCHLOROTHIAZIDE 25 mg/1 1
INACTIVE INGREDIENTS: TITANIUM DIOXIDE; MICROCRYSTALLINE CELLULOSE; LACTOSE MONOHYDRATE; HYPROMELLOSE, UNSPECIFIED; FD&C BLUE NO. 1; STARCH, CORN; MAGNESIUM STEARATE; SILICON DIOXIDE; HYDROXYPROPYL CELLULOSE (1600000 WAMW); D&C YELLOW NO. 10

LOSARTAN POTASSIUM/HCTZ

INDICATIONS AND USAGE

1.1 Hypertension

Losartan potassium and hydrochlorothiazide tablets are indicated for the treatment of hypertension, to lower blood pressure. Lowering blood pressure lowers the risk of fatal and non-fatal cardiovascular (CV) events, primarily strokes and myocardial infarction. These benefits have been seen in controlled trials of antihypertensive drugs from a wide variety of pharmacologic classes including losartan and hydrochlorothiazide.

Control of high blood pressure should be part of comprehensive cardiovascular risk management, including, as appropriate, lipid control, diabetes management, antithrombotic therapy, smoking cessation, exercise, and limited sodium intake. Many patients will require more than 1 drug to achieve blood pressure goals. For specific advice on goals and management, see published guidelines, such as those of the National High Blood Pressure Education Program’s Joint National Committee on Prevention, Detection, Evaluation, and Treatment of High Blood Pressure (JNC).

Numerous antihypertensive drugs, from a variety of pharmacologic classes and with different mechanisms of action, have been shown in randomized controlled trials to reduce cardiovascular morbidity and mortality, and it can be concluded that it is blood pressure reduction, and not some other pharmacologic property of the drugs, that is largely responsible for those benefits. The largest and most consistent cardiovascular outcome benefit has been a reduction in the risk of stroke, but reductions in myocardial infarction and cardiovascular mortality also have been seen regularly.

Elevated systolic or diastolic pressure causes increased cardiovascular risk, and the absolute risk increase per mmHg is greater at higher blood pressures, so that even modest reductions of severe hypertension can provide substantial benefit. Relative risk reduction from blood pressure reduction is similar across populations with varying absolute risk, so the absolute benefit is greater in patients who are at higher risk independent of their hypertension (for example, patients with diabetes or hyperlipidemia), and such patients would be expected to benefit from more aggressive treatment to a lower blood pressure goal.

Some antihypertensive drugs have smaller blood pressure effects (as monotherapy) in Black patients, and many antihypertensive drugs have additional approved indications and effects (e.g., on angina, heart failure, or diabetic kidney disease). These considerations may guide selection of therapy.

This fixed dose combination is not indicated for initial therapy of hypertension, except when the hypertension is severe enough that the value of achieving prompt blood pressure control exceeds the risk of initiating combination therapy in these patients [see Clinical Studies (14) and Dosage and Administration (2.1)].

Losartan potassium and hydrochlorothiazide tablets may be administered with other antihypertensive agents.

1.2 Hypertensive Patients with Left Ventricular Hypertrophy

Losartan potassium and hydrochlorothiazide tablets are indicated to reduce the risk of stroke in patients with hypertension and left ventricular hypertrophy, but there is evidence that this benefit does not apply to Black patients. [See Use in Specific Populations (8.6), Clinical Pharmacology (12.3), and Dosage and Administration (2.2).]

DOSAGE AND ADMINISTRATION

2.1 Hypertension

The usual starting dose of losartan potassium and hydrochlorothiazide tablets is 50/12.5 (losartan 50 mg/hydrochlorothiazide 12.5 mg) once daily. The dosage can be increased after 3 weeks of therapy to a maximum of 100/25 (losartan 100 mg/hydrochlorothiazide 25 mg) once daily as needed to control blood pressure [see Clinical Studies (14.2)].

Initiate a patient whose blood pressure is not adequately controlled with losartan 50 mg monotherapy with losartan potassium and hydrochlorothiazide tablets 50/12.5 once daily. If blood pressure remains uncontrolled after about 3 weeks of therapy, the dosage may be increased to two tablets of losartan potassium and hydrochlorothiazide tablets 50/12.5 once daily or one tablet of losartan potassium and hydrochlorothiazide tablets 100/25 once daily.

Initiate a patient whose blood pressure is not adequately controlled with losartan 100 mg monotherapy with losartan potassium and hydrochlorothiazide tablets 100/12.5 (losartan 100 mg/hydrochlorothiazide 12.5 mg) once daily. If blood pressure remains uncontrolled after about 3 weeks of therapy, increase the dose to two tablets of losartan potassium and hydrochlorothiazide tablets 50/12.5 once daily or one tablet of losartan potassium and hydrochlorothiazide tablets 100/25 once daily.

Initiate a patient whose blood pressure is inadequately controlled with hydrochlorothiazide 25 mg once daily, or is controlled but who experiences hypokalemia with this regimen, on losartan potassium and hydrochlorothiazide tablets 50/12.5 once daily, reducing the dose of hydrochlorothiazide without reducing the overall expected antihypertensive response. Evaluate the clinical response to losartan potassium and hydrochlorothiazide tablets 50/12.5 and, if blood pressure remains uncontrolled after about 3 weeks of therapy, increase the dose to two tablets of losartan potassium and hydrochlorothiazide tablets 50/12.5 once daily or one tablet of losartan potassium and hydrochlorothiazide tablets 100/25 once daily.

2.2 Hypertensive Patients with Left Ventricular Hypertrophy

In patients whose blood pressure is not adequately controlled on 50 mg losartan potassium, initiate treatment with losartan potassium and hydrochlorothiazide tablets 50/12.5. If additional blood pressure reduction is needed, increase the dose to losartan potassium and hydrochlorothiazide tablets 100/12.5, followed by losartan potassium and hydrochlorothiazide tablets 100/25. For further blood pressure reduction add other antihypertensives [see Clinical Studies (14)].

DOSAGE AND ADMINISTRATION

Losartan potassium and hydrochlorothiazide tablets, USP 50/12.5 are yellow, capsule-shaped, film-coated tablets, debossed with “HH” on one side and “211” on the other side.
•
Losartan potassium and hydrochlorothiazide tablets, USP 100/12.5 are white to off-white, capsule-shaped, film-coated tablets, debossed with “HH” on one side and “213” on the other side.
•
Losartan potassium and hydrochlorothiazide tablets, USP 100/25 are yellow, capsule-shaped, film-coated tablets, debossed with “HH” on one side and “212” on the other side.

CONTRAINDICATIONS

Losartan potassium and hydrochlorothiazide tablets are contraindicated:

•
In patients who are hypersensitive to any component of this product.
•
In patients with anuria
•
For coadministration with aliskiren in patients with diabetes

WARNINGS AND PRECAUTIONS

5.1 Fetal Toxicity

Losartan potassium and hydrochlorothiazide tablets can cause fetal harm when administered to a pregnant woman. Use of drugs that act on the renin-angiotensin system during the second and third trimesters of pregnancy reduces fetal renal function and increases fetal and neonatal morbidity and death. Resulting oligohydramnios can be associated with fetal lung hypoplasia and skeletal deformations. Potential neonatal adverse effects include skull hypoplasia, anuria, hypotension, renal failure, and death. When pregnancy is detected, discontinue losartan potassium and hydrochlorothiazide tablets as soon as possible.

Thiazides cross the placental barrier and appear in cord blood. Adverse reactions include fetal or neonatal jaundice, thrombocytopenia [see Use in Specific Populations (8.1)].

5.2 Hypotension in Volume-or Salt-Depleted Patients

In patients with an activated renin-angiotensin system, such as volume-or salt-depleted patients (e.g., those being treated with high doses of diuretics), symptomatic hypotension may occur after initiation of treatment with losartan potassium and hydrochlorothiazide tablets. Correct volume or salt depletion prior to administration of losartan potassium and hydrochlorothiazide tablets. Do not use losartan potassium and hydrochlorothiazide tablets as initial therapy in patients with intravascular volume depletion.

5.3 Impaired Renal Function

Changes in renal function including acute renal failure can be caused by drugs that inhibit the renin-angiotensin system and by diuretics. Patients whose renal function may depend in part on the activity of the renin-angiotensin system (e.g., patients with renal artery stenosis, chronic kidney disease, severe congestive heart failure, or volume depletion) may be at particular risk of developing acute renal failure on losartan potassium and hydrochlorothiazide tablets. Monitor renal function periodically in these patients. Consider withholding or discontinuing therapy in patients who develop a clinically significant decrease in renal function on losartan potassium and hydrochlorothiazide tablets [see Drug Interactions (7.3) and Use in Specific Populations (8.8)].

5.4 Hypersensitivity

Hypersensitivity reactions to hydrochlorothiazide may occur in patients with or without a history of allergy or bronchial asthma, but are more likely in patients with such a history.

5.5 Electrolyte and Metabolic Effects

In double-blind clinical trials of various doses of losartan potassium and hydrochlorothiazide, the incidence of hypertensive patients who developed hypokalemia (serum potassium <3.5 mEq/L) was 6.7% versus 3.5% for placebo; the incidence of hyperkalemia (serum potassium >5.7 mEq/L) was 0.4% versus 0% for placebo.

Losartan potassium and hydrochlorothiazide tablets contain hydrochlorothiazide which can cause hypokalemia, hyponatremia and hypomagnesemia. Hypomagnesemia can result in hypokalemia which may be difficult to treat despite potassium repletion. Losartan potassium and hydrochlorothiazide tablets also contain losartan which can cause hyperkalemia. Monitor serum electrolytes periodically [see Drug Interactions (7.1)].

Concomitant use of other drugs that may increase serum potassium may lead to hyperkalemia [see Drug Interactions (7.1)].

Hydrochlorothiazide may alter glucose tolerance and raise serum levels of cholesterol and triglycerides.

Hyperuricemia may occur or frank gout may be precipitated in patients receiving thiazide therapy. Because losartan decreases uric acid, losartan in combination with hydrochlorothiazide attenuates the diuretic-induced hyperuricemia.

Hydrochlorothiazide decreases urinary calcium excretion and may cause elevations of serum calcium. Monitor calcium levels.

5.6 Acute Myopia and Secondary Angle-Closure Glaucoma

Hydrochlorothiazide, a sulfonamide, can cause an idiosyncratic reaction, resulting in acute transient myopia and acute angle-closure glaucoma. Symptoms include acute onset of decreased visual acuity or ocular pain and typically occur within hours to weeks of drug initiation. Untreated acute angle-closure glaucoma can lead to permanent vision loss. The primary treatment is to discontinue hydrochlorothiazide as rapidly as possible. Prompt medical or surgical treatments may need to be considered if the intraocular pressure remains uncontrolled. Risk factors for developing acute angle-closure glaucoma may include a history of sulfonamide or penicillin allergy.

5.7 Systemic Lupus Erythematosus

Thiazide diuretics have been reported to cause exacerbation or activation of systemic lupus erythematosus.

ADVERSE REACTIONS

6.1 Clinical Trials Experience

Because clinical trials are conducted under widely varying conditions, adverse reaction rates observed in the clinical trials of a drug cannot be directly compared to rates in the clinical trials of another drug and may not reflect the rates observed in practice.

Losartan potassium-hydrochlorothiazide has been evaluated for safety in 858 patients treated for essential hypertension and 3889 patients treated for hypertension and left ventricular hypertrophy. Most adverse reactions have been mild and transient in nature and have not required discontinuation of therapy. In controlled clinical trials, discontinuation of therapy due to clinical adverse events was required in only 2.8% and 2.3% of patients treated with the combination and placebo, respectively.

In these double-blind controlled clinical trials, adverse reactions occurring in greater than 2% of subjects treated with losartan-hydrochlorothiazide and at a greater rate than placebo were: back pain (2.1% vs 0.6%), dizziness (5.7% vs 2.9%), and upper respiratory infection (6.1% vs 4.6%).

The following additional adverse reactions have been reported in clinical trials with losartan potassium and hydrochlorothiazide tablets and/or the individual components:

Blood and the lymphatic system disorders: Anemia, aplastic anemia, hemolytic anemia, leukopenia, agranulocytosis.

Metabolism and nutrition disorders: Anorexia, hyperglycemia, hyperuricemia, electrolyte imbalance including hyponatremia and hypokalemia.

Psychiatric disorders: Insomnia, restlessness.

Nervous system disorders: Dysgeusia, headache, migraine, paraesthesias.

Eye disorders: Xanthopsia, transient blurred vision.

Cardiac disorders: Palpitation, tachycardia.

Vascular disorders: Dose-related orthostatic effects, necrotizing angiitis (vasculitis, cutaneous vasculitis).

Respiratory, thoracic and mediastinal disorders: Nasal congestion.

Gastrointestinal disorders: Dyspepsia, abdominal pain, gastric irritation, cramping, nausea, vomiting, pancreatitis, sialoadenitis.

Hepato-biliary disorders: Jaundice (intrahepatic cholestatic jaundice).

Skin and subcutaneous tissue disorders: Rash, pruritus, purpura, toxic epidermal necrolysis, urticaria, photosensitivity, cutaneous lupus erythematosus.

Musculoskeletal and connective tissue disorders: Muscle cramps, muscle spasm.

Renal and urinary disorders: Glycosuria, renal dysfunction, interstitial nephritis, renal failure.

Reproductive system and breast disorders: Erectile dysfunction/impotence.

General disorders and administration site conditions: Chest pain, malaise, weakness.

Investigations: Liver function abnormalities.

Cough

Persistent dry cough has been associated with ACE-inhibitor use and in practice can be a cause of discontinuation of ACE-inhibitor therapy. Two prospective, parallel-group, double-blind, randomized, controlled trials were conducted to assess the effects of losartan on the incidence of cough in hypertensive patients who had experienced cough while receiving ACE-inhibitor therapy. Patients who had typical ACE-inhibitor cough when challenged with lisinopril, whose cough disappeared on placebo, were randomized to losartan 50 mg, lisinopril 20 mg, or either placebo (one study, n=97) or 25 mg hydrochlorothiazide (n=135). The double-blind treatment period lasted up to 8 weeks. The incidence of cough is shown in Table 1 below.

Table 1:

Study 1*

HCTZ

Losartan

Lisinopril

Cough

25%

17%

69%

Study 2†

Placebo

Losartan

Lisinopril

Cough

35%

29%

62%

* Demographics = (89% Caucasian, 64% female)

† Demographics = (90% Caucasian, 51% female)

These studies demonstrate that the incidence of cough associated with losartan therapy, in a population that all had cough associated with ACE-inhibitor therapy, is similar to that associated with hydrochlorothiazide or placebo therapy.

Cases of cough, including positive re-challenges, have been reported with the use of losartan in postmarketing experience.

6.2 Postmarketing Experience

The following adverse reactions have been identified during post-approval use of losartan potassium and hydrochlorothiazide tablets. Because these reactions are reported voluntarily from a population of uncertain size, it is not always possible to estimate their frequency reliably or to establish a causal relationship to drug exposure.

Digestive: Hepatitis has been reported rarely in patients treated with losartan.

Hematologic: Thrombocytopenia.

Hypersensitivity: Angioedema, including swelling of the larynx and glottis, causing airway obstruction and/or swelling of the face, lips, pharynx, and/or tongue has been reported rarely in patients treated with losartan; some of these patients previously experienced angioedema with other drugs including ACE inhibitors. Vasculitis, including Henoch-Schönlein purpura, has been reported with losartan. Anaphylactic reactions have been reported.

Musculoskeletal: Rhabdomyolysis.

Skin: Erythroderma.

Non-melanoma Skin Cancer: Hydrochlorothiazide is associated with an increased risk of non-melanoma skin cancer. In a study conducted in the Sentinel System, increased risk was predominantly for squamous cell carcinoma (SCC) and in white patients taking large cumulative doses. The increased risk for SCC in the overall population was approximately 1 additional case per 16,000 patients per year, and for white patients taking a cumulative dose of ≥50,000mg the risk increase was approximately 1 additional SCC case for every 6,700 patients per year.

DRUG INTERACTIONS

7.1 Agents Increasing Serum Potassium

Coadministration of losartan with other drugs that raise serum potassium levels may result in hyperkalemia. Monitor serum potassium in such patients.

7.2 Lithium

Increases in serum lithium concentrations and lithium toxicity have been reported with concomitant use of angiotensin II receptor antagonists or thiazide diuretics. Monitor lithium levels in patients receiving losartan potassium and hydrochlorothiazide tablets and lithium.

7.3 Non-Steroidal Anti-Inflammatory Agents Including Selective Cyclooxygenase-2 Inhibitors

Losartan Potassium

In patients who are elderly, volume-depleted (including those on diuretic therapy), or with compromised renal function, coadministration of NSAIDs, including selective COX-2 inhibitors, with angiotensin II receptor antagonists (including losartan) may result in deterioration of renal function, including possible acute renal failure. These effects are usually reversible. Monitor renal function periodically in patients receiving losartan and NSAID therapy.

The antihypertensive effect of angiotensin II receptor antagonists, including losartan, may be attenuated by NSAIDs, including selective COX-2 inhibitors.

Hydrochlorothiazide

The administration of a non-steroidal anti-inflammatory agent including a selective COX-2 inhibitor can reduce the diuretic, natriuretic, and antihypertensive effects of loop, potassium-sparing and thiazide diuretics. Therefore, when losartan potassium and hydrochlorothiazide tablets and non-steroidal anti-inflammatory agents including selective COX-2 inhibitors are used concomitantly, observe closely to determine if the desired effect of the diuretic is obtained.

In patients receiving diuretic therapy, coadministration of NSAIDs with angiotensin receptor blockers, including losartan, may result in deterioration of renal function, including possible acute renal failure. These effects are usually reversible. Monitor renal function periodically in patients receiving hydrochlorothiazide, losartan, and NSAID therapy.

7.4 Dual Blockade of the Renin-Angiotensin System (RAS)

Dual blockade of the RAS with angiotensin receptor blockers, ACE inhibitors, or aliskiren is associated with increased risks of hypotension, syncope, hyperkalemia, and changes in renal function (including acute renal failure) compared to monotherapy.

The Veterans Affairs Nephropathy in Diabetes (VA NEPHRON-D) trial enrolled 1448 patients with type 2 diabetes, elevated urinary-albumin-to-creatinine ratio, and decreased estimated glomerular filtration rate (GFR 30 to 89.9 mL/min), randomized them to lisinopril or placebo on a background of losartan therapy and followed them for a median of 2.2 years. Patients receiving the combination of losartan and lisinopril did not obtain any additional benefit compared to monotherapy for the combined endpoint of decline in GFR, end-stage renal disease, or death, but experienced an increased incidence of hyperkalemia and acute kidney injury compared with the monotherapy group.

Closely monitor blood pressure, renal function, and electrolytes in patients on losartan potassium and hydrochlorothiazide tablets and other agents that affect the RAS.

Do not coadminister aliskiren with losartan potassium and hydrochlorothiazide tablets in patients with diabetes. Avoid use of aliskiren with losartan potassium and hydrochlorothiazide tablets in patients with renal impairment (GFR <60 mL/min).

7.5 The Use of Hydrochlorothiazide with Other Drugs

When administered concurrently, the following drugs may interact with thiazide diuretics [see Clinical Pharmacology (12.3)]:

Antidiabetic drugs (oral agents and insulin) — dosage adjustment of the antidiabetic drug may be required.

Cholestyramine and colestipol resins — Absorption of hydrochlorothiazide is impaired in the presence of anionic exchange resins. Single doses of either cholestyramine or colestipol resins bind the hydrochlorothiazide and reduce its absorption from the gastrointestinal tract by up to 85 and 43 percent, respectively. Stagger the dosage of hydrochlorothiazide and the resin such that hydrochlorothiazide is administered at least 4 hours before or 4 to 6 hours after the administration of the resin.

USE IN SPECIFIC POPULATIONS

8.1 Pregnancy

Risk Summary

Losartan potassium and hydrochlorothiazide tablets can cause fetal harm when administered to a pregnant woman. Use of drugs that act on the renin-angiotensin system during the second and third trimesters of pregnancy reduces fetal renal function and increases fetal and neonatal morbidity and death. Most epidemiologic studies examining fetal abnormalities after exposure to antihypertensive use in the first trimester have not distinguished drugs affecting the renin-angiotensin system from other antihypertensive agents. When pregnancy is detected, discontinue losartan potassium and hydrochlorothiazide tablets as soon as possible (see Clinical Considerations).

The estimated background risk of major birth defects and miscarriage for the indicated population is unknown. All pregnancies have a background risk of birth defect, loss, or other adverse outcomes. In the U.S. general population, the estimated background risk of major birth defects and miscarriage in clinically recognized pregnancies is 2% to 4% and 15% to 20%, respectively.

Clinical Considerations

Disease associated Maternal and/or Embryo/Fetal Risk Hypertension in pregnancy increases the maternal risk for pre-eclampsia, gestational diabetes, premature delivery, and delivery complications (e.g., need for cesarean section, post-partum hemorrhage). Hypertension increases the fetal risk for intrauterine growth restriction and intrauterine death. Pregnant women with hypertension should be carefully monitored and managed accordingly.

Fetal/Neonatal Adverse Reactions

Losartan:

Use of drugs that act on the renin-angiotensin system in the second and third trimesters of pregnancy can result in the following: oligohydramnios, reduced fetal renal function leading to anuria and renal failure, fetal lung hypoplasia, skeletal deformations, including skull hypoplasia, hypotension, and death. In the unusual case that there is no appropriate alternative to therapy with drugs affecting the renin-angiotensin system for a particular patient, apprise the mother of the potential risk to the fetus. Perform serial ultrasound examinations to assess the intra-amniotic environment. If oligohydramnios is observed, discontinue losartan potassium and hydrochlorothiazide tablets, unless it is considered lifesaving for the mother. Fetal testing may be appropriate, based on the week of gestation. Patients and physicians should be aware, however, that oligohydramnios may not appear until after the fetus has sustained irreversible injury. Closely observe infants with histories of in utero exposure to losartan potassium and hydrochlorothiazide tablets for hypotension, oliguria, and hyperkalemia. In neonates with a history of in utero exposure to losartan potassium and hydrochlorothiazide tablets, if oliguria or hypotension occurs, support blood pressure and renal perfusion. Exchange transfusions or dialysis may be required as a means of reversing hypotension and replacing renal function.

Hydrochlorothiazide:

Thiazides can cross the placenta, and concentrations reached in the umbilical vein approach those in the maternal plasma. Hydrochlorothiazide, like other diuretics, can cause placental hypoperfusion. It accumulates in the amniotic fluid, with reported concentrations up to 19 times higher than in umbilical vein plasma. Use of thiazides during pregnancy is associated with a risk of fetal or neonatal jaundice or thrombocytopenia. Since they do not alter the course of pre-eclampsia, these drugs should not be used to treat hypertension in pregnant women. The use of hydrochlorothiazide for other indications in pregnancy should be avoided.

Data

Animal Data

There was no evidence of teratogenicity in rats or rabbits treated with a maximum losartan potassium dose of 10 mg/kg/day in combination with 2.5 mg/kg/day of hydrochlorothiazide. At these dosages, respective exposures (AUCs) of losartan, its active metabolite, and hydrochlorothiazide in rabbits were approximately 5, 1.5, and 1.0 times those achieved in humans with 100 mg losartan in combination with 25 mg hydrochlorothiazide. AUC values for losartan, its active metabolite and hydrochlorothiazide, extrapolated from data obtained with losartan administered to rats at a dose of 50 mg/kg/day in combination with 12.5 mg/kg/day of hydrochlorothiazide, were approximately 6, 2, and 2 times greater than those achieved in humans with 100 mg of losartan in combination with 25 mg of hydrochlorothiazide. Fetal toxicity in rats, as evidenced by a slight increase in supernumerary ribs, was observed when females were treated prior to and throughout gestation with 10 mg/kg/day losartan in combination with 2.5 mg/kg/day hydrochlorothiazide. As also observed in studies with losartan alone, adverse fetal and neonatal effects, including decreased body weight, renal toxicity, and mortality, occurred when pregnant rats were treated during late gestation and/or lactation with 50 mg/kg/day losartan in combination with 12.5 mg/kg/day hydrochlorothiazide. Respective AUCs for losartan, its active metabolite and hydrochlorothiazide at these dosages in rats were approximately 35, 10 and 10 times greater than those achieved in humans with the administration of 100 mg of losartan in combination with 25 mg hydrochlorothiazide. When hydrochlorothiazide was administered without losartan to pregnant mice and rats during their respective periods of major organogenesis, at doses up to 3000 and 1000 mg/kg/day, respectively, there was no evidence of harm to the fetus.

8.2 Lactation

Risk Summary

It is not known whether losartan is excreted in human milk, but significant levels of losartan and its active metabolite were shown to be present in rat milk. Thiazides appear in human milk. Because of the potential for adverse effects on the nursing infant, a decision should be made whether to discontinue nursing or discontinue the drug, taking into account the importance of the drug to the mother.

8.4 Pediatric Use

Safety and effectiveness of losartan potassium and hydrochlorothiazide tablets in pediatric patients have not been established.

Neonates with a history of in utero exposure to losartan potassium and hydrochlorothiazide tablets: If oliguria or hypotension occurs, direct attention toward support of blood pressure and renal perfusion. Exchange transfusion or dialysis may be required as means of reversing hypotension and/or substituting for disordered renal function.

8.5 Geriatric Use

In a controlled clinical study for the reduction in the combined risk of cardiovascular death, stroke and myocardial infarction in hypertensive patients with left ventricular hypertrophy, 2857 patients (62%) were 65 years and over, while 808 patients (18%) were 75 years and over. In an effort to control blood pressure in this study, patients were coadministered losartan and hydrochlorothiazide 74% of the total time they were on study drug. No overall differences in effectiveness were observed between these patients and younger patients. Adverse events were somewhat more frequent in the elderly compared to non-elderly patients for both the losartan-hydrochlorothiazide and the control groups [see Clinical Pharmacology (12.3)].

8.6 Race

In the Losartan Intervention For Endpoint reduction in hypertension (LIFE) study, Black patients with hypertension and left ventricular hypertrophy treated with atenolol had a lower risk of stroke, the primary composite endpoint, as compared with Black patients treated with losartan (both cotreated with hydrochlorothiazide in the majority of patients). In the subgroup of Black patients (n=533, 6% of the LIFE study patients), there were 29 primary endpoints among 263 patients on atenolol (11%, 26 per 1000 patient-years) and 46 primary endpoints among 270 patients (17%, 42 per 1000 patient-years) on losartan. This finding could not be explained on the basis of differences in the populations other than race or on any imbalances between treatment groups. In addition, blood pressure reductions in both treatment groups were consistent between Black and non-Black patients. Given the difficulty in interpreting subset differences in large trials, it cannot be known whether the observed difference is the result of chance. However, the LIFE study provides no evidence that the benefits of losartan on reducing the risk of cardiovascular events in hypertensive patients with left ventricular hypertrophy apply to Black patients [see Clinical Pharmacology (12.3)].

8.7 Hepatic Impairment

Initiation of losartan potassium and hydrochlorothiazide tablets is not recommended for patients with hepatic impairment because the appropriate starting dose of losartan, 25 mg, is not available.

8.8 Renal Impairment

Changes in renal function have been reported in susceptible individuals [see Dosage and Administration (2.1), Warnings and Precautions (5.4), and Clinical Pharmacology (12.3)]. Safety and effectiveness of losartan potassium and hydrochlorothiazide tablets in patients with severe renal impairment (creatinine clearance <30 mL/min) have not been established.

DESCRIPTION

Losartan potassium and hydrochlorothiazide tablets, 50/12.5 mg, losartan potassium and hydrochlorothiazide tablets, 100/12.5 mg and losartan potassium and hydrochlorothiazide tablets, 100/25 mg combine an angiotensin II receptor blocker acting on the AT1 receptor subtype and a diuretic, hydrochlorothiazide.

Losartan potassium, a non-peptide molecule, is chemically described as 2-butyl-4-chloro-1-[p-(o-1H-tetrazol-5-ylphenyl)benzyl]imidazole-5-methanol monopotassium salt. Its empirical formula is C22H22ClKN6O, and its structural formula is:

73c71ed3-figure-01
Losartan potassium is a white to off-white free-flowing crystalline powder with a molecular weight of 461.01. It is freely soluble in water, soluble in alcohols, and slightly soluble in common organic solvents, such as acetonitrile and methyl ethyl ketone.

Oxidation of the 5-hydroxymethyl group on the imidazole ring results in the active metabolite of losartan.

Hydrochlorothiazide is 6-chloro-3,4-dihydro-2H-1,2,4-benzothiadiazine-7-sulfonamide 1,1-dioxide. Its empirical formula is C7H8ClN3O4S2 and its structural formula is:

73c71ed3-figure-02
Hydrochlorothiazide is a white, or practically white, crystalline powder with a molecular weight of 297.74, which is slightly soluble in water, but freely soluble in sodium hydroxide solution.

Losartan potassium and hydrochlorothiazide tablets, USP are available for oral administration in three tablet combinations of losartan and hydrochlorothiazide. Losartan potassium and hydrochlorothiazide tablets 50/12.5 mg contain 50 mg of losartan potassium and 12.5 mg of hydrochlorothiazide. Losartan potassium and hydrochlorothiazide tablets 100/12.5 mg contain 100 mg of losartan potassium and 12.5 mg of hydrochlorothiazide. Losartan potassium and hydrochlorothiazide tablets 100/25 mg contain 100 mg of losartan potassium and 25 mg of hydrochlorothiazide. Inactive ingredients are microcrystalline cellulose, lactose monohydrate, pregelatinized starch, magnesium stearate, colloidal silicon dioxide, hydroxypropyl cellulose, hypromellose, and titanium dioxide. Losartan potassium and hydrochlorothiazide tablets 50/12.5 mg and 100/25 mg also contain D&C yellow No. 10 aluminum lake and FD&C blue No. 1/brilliant blue FCF aluminum lake.

Losartan potassium and hydrochlorothiazide tablets 50/12.5 mg contain 4.24 mg (0.108 mEq) of potassium, losartan potassium and hydrochlorothiazide tablets 100/12.5 mg contain 8.48 mg (0.216 mEq) of potassium, and losartan potassium and hydrochlorothiazide tablets 100/25 mg contain 8.48 mg (0.216 mEq) of potassium.

OVERDOSAGE

Losartan Potassium

Significant lethality was observed in mice and rats after oral administration of 1000 mg/kg and 2000 mg/kg, respectively, about 44 and 170 times the maximum recommended human dose on a mg/m2 basis.

Limited data are available in regard to overdosage in humans. The most likely manifestation of overdosage would be hypotension and tachycardia; bradycardia could occur from parasympathetic (vagal) stimulation. If symptomatic hypotension should occur, supportive treatment should be instituted.

Neither losartan nor its active metabolite can be removed by hemodialysis.

Hydrochlorothiazide

The oral LD50 of hydrochlorothiazide is greater than 10 g/kg in both mice and rats. The most common signs and symptoms observed are those caused by electrolyte depletion (hypokalemia, hypochloremia, hyponatremia) and dehydration resulting from excessive diuresis. If digitalis has also been administered, hypokalemia may accentuate cardiac arrhythmias. The degree to which hydrochlorothiazide is removed by hemodialysis has not been established.

HOW SUPPLIED

Losartan potassium and hydrochlorothiazide tablets, USP are supplied as a film-coated tablet.

Losartan/ Hydrochlorothiazide

Color

Shape

Engraving

NDC 43547-xxx-xx

Bottle/ 30

Bottle/ 90

Bottle/ 1000

50/12.5 mg

yellow

capsule-shaped

HH/211

423-03

423-09

423-11

100/12.5 mg

white to off-white

capsule-shaped

HH/213

425-03

425-09

425-11

100/25 mg

yellow

capsule-shaped

HH/212

424-03

424-09

424-11

Store at 20°C to 25°C (68°F to 77°F); excursions permitted to 15°C to 30°C (59°F to 86°F) [see USP Controlled Room Temperature]. Keep container tightly closed. Protect from light.